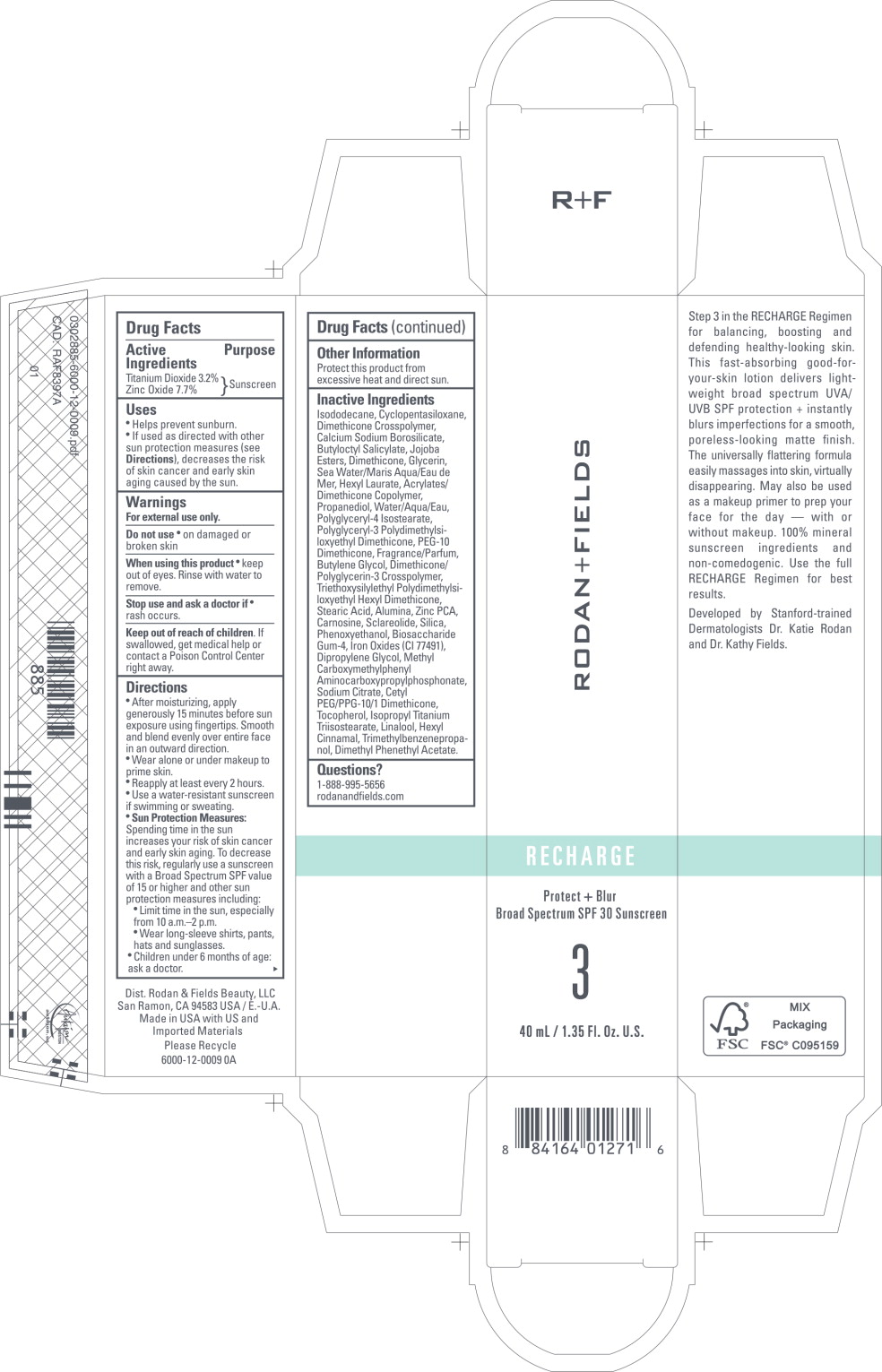 DRUG LABEL: RECHARGE Protect Blur
NDC: 14222-8010 | Form: CREAM
Manufacturer: Rodan & Fields Beauty, LLC
Category: otc | Type: HUMAN OTC DRUG LABEL
Date: 20251208

ACTIVE INGREDIENTS: TITANIUM DIOXIDE 0.032 g/1 mL; ZINC OXIDE 0.077 g/1 mL
INACTIVE INGREDIENTS: ISODODECANE; CYCLOMETHICONE 5; DIMETHICONE CROSSPOLYMER; CALCIUM SODIUM BOROSILICATE; BUTYLOCTYL SALICYLATE; HYDROGENATED JOJOBA OIL/JOJOBA OIL, RANDOMIZED (IODINE VALUE 64-70); DIMETHICONE, UNSPECIFIED; GLYCERIN; SODIUM CHLORIDE; HEXYL LAURATE; ACRYLIC ACID/DIMETHICONE METHACRYLATE/ETHYLHEXYL ACRYLATE COPOLYMER; PROPANEDIOL; WATER; POLYGLYCERYL-4 ISOSTEARATE; POLYGLYCERYL-3 POLYDIMETHYLSILOXYETHYL DIMETHICONE (4000 MPA.S); DIMETHICONE PEG-10 PHOSPHATE; BUTYLENE GLYCOL; DIMETHICONE/POLYGLYCERIN-3 CROSSPOLYMER; TRIETHOXYSILYLETHYL POLYDIMETHYLSILOXYETHYL HEXYL DIMETHICONE; STEARIC ACID; ALUMINUM OXIDE; ZINC PIDOLATE; CARNOSINE; SCLAREOLIDE; SILICON DIOXIDE; PHENOXYETHANOL; BIOSACCHARIDE GUM-4; FERRIC OXIDE RED; DIPROPYLENE GLYCOL; METHYL CARBOXYMETHYLPHENYL AMINOCARBOXYPROPYLPHOSPHONATE; SODIUM CITRATE, UNSPECIFIED FORM; CETYL PEG/PPG-10/1 DIMETHICONE (HLB 3); TOCOPHEROL; ISOPROPYL TITANIUM TRIISOSTEARATE; LINALOOL, (+/-)-; .ALPHA.-HEXYLCINNAMALDEHYDE; TRIMETHYLBENZENEPROPANOL; DIMETHYL BENZYL CARBINYL ACETATE

Drug Facts

Active Ingredients

Titanium Dioxide 3.2%

Zinc Oxide 7.7%

Purpose

Sunscreen

Sunscreen

Uses

- Helps prevent sunburn.
- If used as directed with other sun protection measures (see Directions), decreases the risk of skin cancer and early skin aging caused by the sun.

Warnings

For external use only.

Do not use

- on damaged or broken skin

When using this product

- keep out of eyes. Rinse with water to remove.

Stop use and ask a doctor if

- rash occurs.

Keep out of reach of children. If swallowed, get medical help or contact a Poison Control Center right away.

Directions

- After moisturizing, apply generously 15 minutes before sun exposure using fingertips. Smooth and blend evenly over entire face in an outward direction.
- Wear alone or under makeup to prime skin.
- Reapply at least every 2 hours.
- Use a water-resistant sunscreen if swimming or sweating.
- Sun Protection Measures:
  Spending time in the sun increases your risk of skin cancer and early skin aging. To decrease this risk, regularly use a sunscreen with a Broad Spectrum SPF value of 15 or higher and other sun protection measures including:
  - Limit time in the sun, especially from 10 a.m.-2 p.m.
  - Wear long-sleeve shirts, pants, hats and sunglasses.
  - Children under 6 months of age: ask a doctor.

Other Information

Protect this product from excessive heat and direct sun.

Inactive Ingredients

Isododecane, Cyclopentasiloxane, Dimethicone Crosspolymer, Calcium Sodium Borosilicate, Butyloctyl Salicylate, Jojoba Esters, Dimethicone, Glycerin, Sea Water/Maris Aqua/Eau de Mer, Hexyl Laurate, Acrylates/ Dimethicone Copolymer, Propanediol, Water/Aqua/Eau, Polyglyceryl-4 Isostearate, Polyglyceryl-3 Polydimethylsiloxyethyl Dimethicone, PEG-10 Dimethicone, Fragrance/Parfum, Butylene Glycol, Dimethicone/ Polyglycerin-3 Crosspolymer, Triethoxysilylethyl Polydimethylsiloxyethyl Hexyl Dimethicone, Stearic Acid, Alumina, Zinc PCA, Carnosine, Sclareolide, Silica, Phenoxyethanol, Biosaccharide Gum-4, Iron Oxides (Cl 77491), Dipropylene Glycol, Methyl Carboxymethylphenyl Aminocarboxypropylphosphonate, Sodium Citrate, Cetyl PEG/PPG-10/1 Dimethicone, Tocopherol, Isopropyl Titanium Triisostearate, Linalool, Hexyl Cinnamal, Trimethylbenzenepropanol, Dimethyl Phenethyl Acetate.

Questions?

1-888-995-5656

rodanandfields.com

Principal Display Panel - 40 mL Carton Label

RODAN + FIELDS

RECHARGE

Protect + Blur
Broad Spectrum SPF 30 Sunscreen

3

40 mL / 1.35 Fl. Oz. U.S.